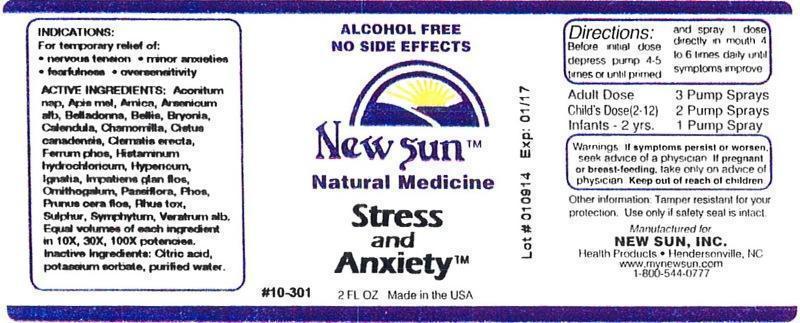 DRUG LABEL: Stress and Anxiety
NDC: 66579-0018 | Form: LIQUID
Manufacturer: New Sun Inc.
Category: homeopathic | Type: HUMAN OTC DRUG LABEL
Date: 20140717

ACTIVE INGREDIENTS: ACONITUM NAPELLUS 10 [hp_X]/59 mL; APIS MELLIFERA 10 [hp_X]/59 mL; ARNICA MONTANA 10 [hp_X]/59 mL; ARSENIC TRIOXIDE 10 [hp_X]/59 mL; ATROPA BELLADONNA 10 [hp_X]/59 mL; BELLIS PERENNIS 10 [hp_X]/59 mL; BRYONIA ALBA ROOT 10 [hp_X]/59 mL; CALENDULA OFFICINALIS FLOWERING TOP 10 [hp_X]/59 mL; MATRICARIA RECUTITA 10 [hp_X]/59 mL; HELIANTHEMUM CANADENSE 10 [hp_X]/59 mL; CLEMATIS RECTA FLOWERING TOP 10 [hp_X]/59 mL; FERROSOFERRIC PHOSPHATE 10 [hp_X]/59 mL; HISTAMINE DIHYDROCHLORIDE 10 [hp_X]/59 mL; HYPERICUM PERFORATUM 10 [hp_X]/59 mL; STRYCHNOS IGNATII SEED 10 [hp_X]/59 mL; IMPATIENS GLANDULIFERA FLOWER 10 [hp_X]/59 mL; ORNITHOGALUM UMBELLATUM 10 [hp_X]/59 mL; PASSIFLORA INCARNATA FLOWERING TOP 10 [hp_X]/59 mL; PHOSPHORUS 10 [hp_X]/59 mL; PRUNUS CERASIFERA FLOWER 10 [hp_X]/59 mL; TOXICODENDRON PUBESCENS LEAF 10 [hp_X]/59 mL; SULFUR 10 [hp_X]/59 mL; COMFREY ROOT 10 [hp_X]/59 mL; VERATRUM ALBUM ROOT 10 [hp_X]/59 mL
INACTIVE INGREDIENTS: CITRIC ACID MONOHYDRATE; POTASSIUM SORBATE; WATER

Stress and Anxiety

DOSAGE AND ADMINISTRATION

Directions: Before initial dose depress pump 4-5 times or until primed and spray 1 dose directly in mouth 4 to 6 times daily until symptoms improve.

Adult Dose: 3 Pump Sprays

Child's Dose (2-12): 2 Pump Sprays

Infants - 2 yrs: 1 Pump Sprays

WARNINGS

Warnings: If symptoms persist or worsen, seek advice of physician. If pregnant or breast-feeding, take only on advice of physician.

Keep out of reach of children.

Other information: Tamper resistant for your protection. Use only if safety seal is intact.

PURPOSE

Indications: For temporary relief of: •nervous tension •minor anxieties •fearfulness •oversenaitivity

ACTIVE INGREDIENT

Active Ingredients: Aconitum napellus, Apis mellifica, Arnica montana, Arsenicum album, Belladonna, Bellis perennis, Bryonia, Calendula officinalis, Chamomilla, Cistus canadensis, Clematis erecta, Ferrum phosphoricum, Histaminum hydrochloricum, Hypericum perforatum, Ignatia amara, Impatiens glandulifera, flos, Ornithogalum umbellatum, Passiflora incarnata, Phosphorus, Prunus cerasifera, flos, Rhus toxicodendron, Sulphur, Symphytum officinale, Veratrum album. Equal volumes of each ingredient in 10X, 30X, 100X potencies.

Inactive Ingredient: Citric acid, potassium sorbate, purified water.

Indications: For temporary relief of:

- nervous tension
- minor anxieties
- fearfulness
- oversensitivity